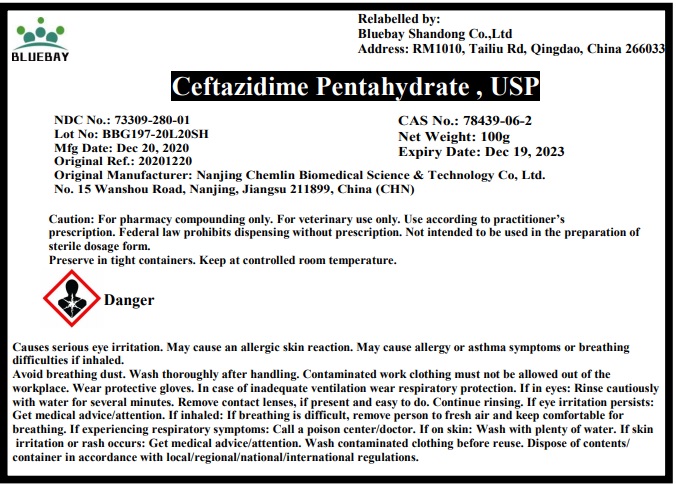 DRUG LABEL: Ceftazidime Pentahydrate
NDC: 73309-280 | Form: POWDER
Manufacturer: BLUEBAY SHANDONG CO.,LTD
Category: other | Type: BULK INGREDIENT
Date: 20210409

ACTIVE INGREDIENTS: CEFTAZIDIME 1 g/1 g

Ceftazidime Pentahydrate